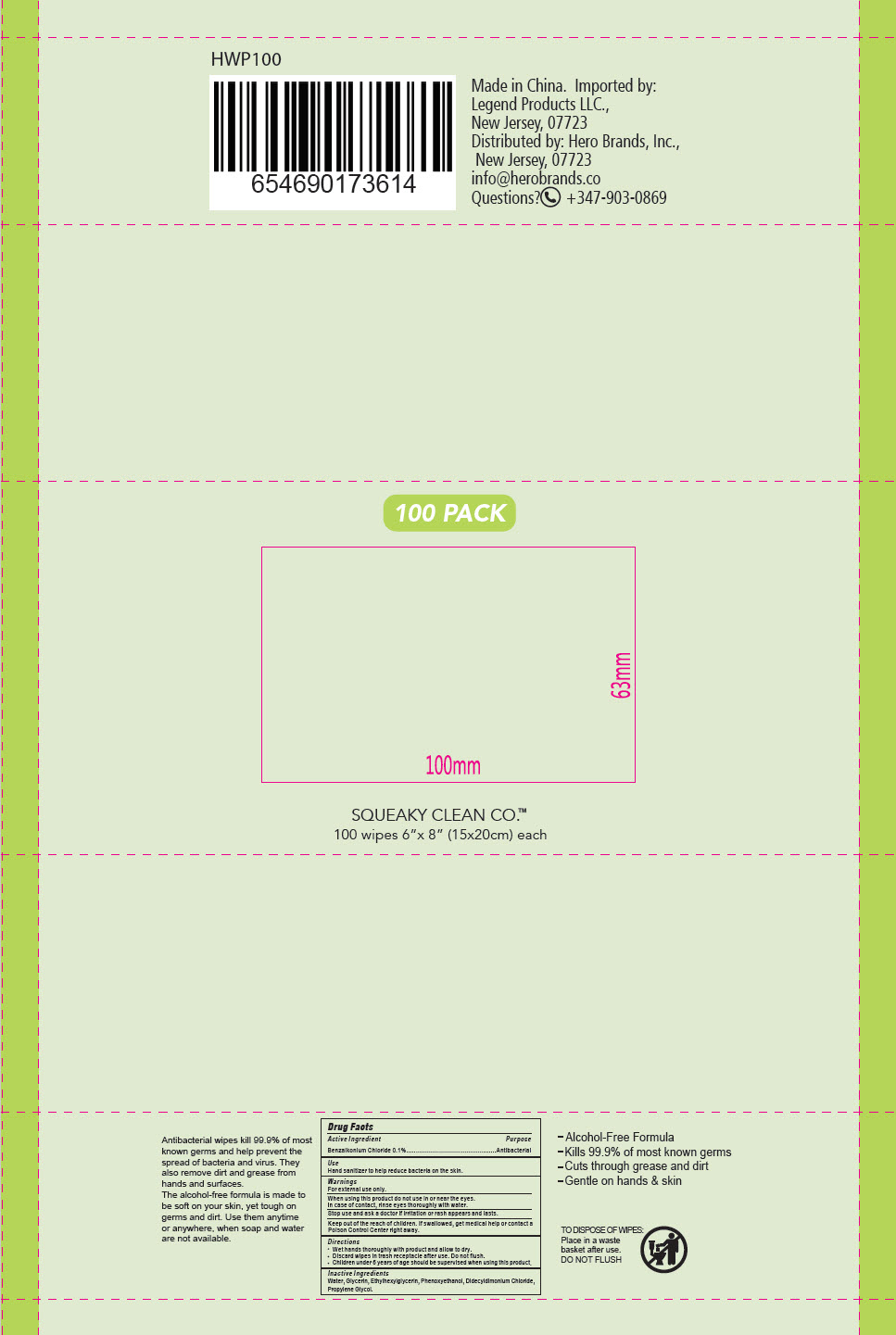 DRUG LABEL: Squeaky Clean Antibacterial Hand Wipes
NDC: 90114-301 | Form: CLOTH
Manufacturer: Hero Brands, Inc.
Category: otc | Type: HUMAN OTC DRUG LABEL
Date: 20200807

ACTIVE INGREDIENTS: BENZALKONIUM CHLORIDE 5.8 g/1 1
INACTIVE INGREDIENTS: WATER; GLYCERIN; ETHYLHEXYLGLYCERIN; PHENOXYETHANOL; DIDECYLDIMONIUM CHLORIDE; PROPYLENE GLYCOL

Squeaky Clean Antibacterial Hand Wipes

Drug Facts

Active Ingredient

Benzalkonium Chloride 0.1%

Purpose

Antibacterial

Use

Hand sanitizer to help reduce bacteria on the skin.

Warnings

For external use only.

When using this product do not use in or near the eyes.

In case of contact, rinse eyes thoroughly with water.

Stop use and ask a doctor if irritation or rash appears and lasts.

KEEP OUT OF REACH OF CHILDREN

Keep out of the reach of children. If swallowed, get medical help or contact a Poison Control Center right away.

Directions

- Wet hands thoroughly with product and allow to dry.
- Discard wipes in trash receptacle after use. Do not flush.
- Children under 6 years of age should be supervised when using this product.

Inactive Ingredients

Water, Glycerin, Ethylhexylglycerin, Phenoxyethanol, Didecyldimonium Chloride, Propylene Glycol.

Questions?

+347-903-0869

Distributed by: Hero Brands, Inc.,
New Jersey, 07723

PRINCIPAL DISPLAY PANEL - 100 Wipe Bag

GOOD
CLEAN
FUN™

ALCOHOL-FREE
FRESH SCENT

ANTIBACTERIAL HAND SANITIZING WIPES
KILLS 99.9% OF GERMS